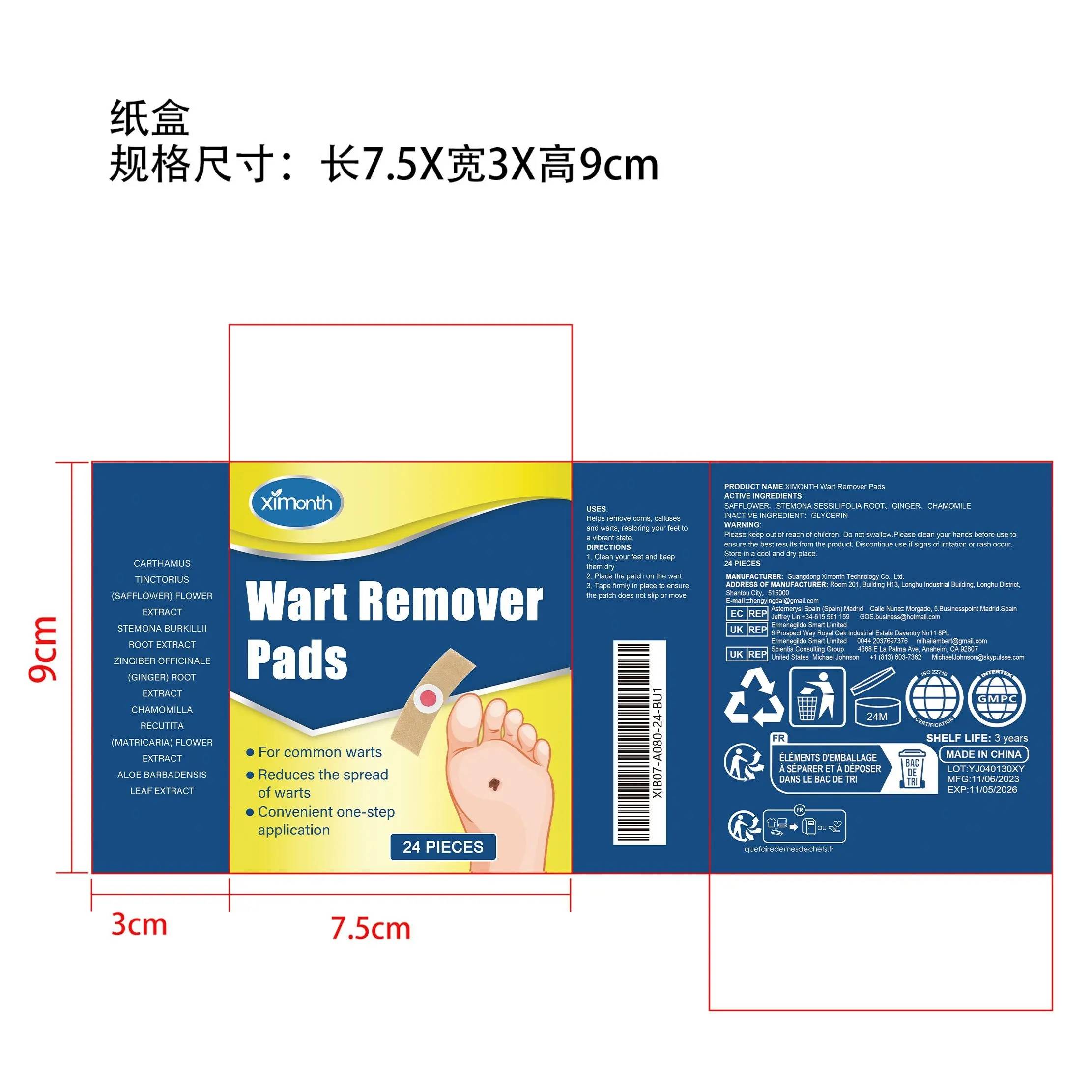 DRUG LABEL: XIMONTH Wart Remover Pads
NDC: 84660-056 | Form: PATCH
Manufacturer: Guangdong Ximonth Technology Co., Ltd.
Category: otc | Type: HUMAN OTC DRUG LABEL
Date: 20241101

ACTIVE INGREDIENTS: STEMONA SESSILIFOLIA ROOT 6 g/30 g; CHAMOMILE 10 g/30 g; GINGER 2 g/30 g; SAFFLOWER 6 g/30 g
INACTIVE INGREDIENTS: GLYCERIN 6 g/30 g

Active Ingredient(s)

SAFFLOWER、STEMONA SESSILIFOLIA ROOT、GINGER、CHAMOMILE

Purpose

Helps remove corns, calluses and warts, restoring your feet to a vibrant state.

Use

1. Clean your feet and keep them dry
2. Place the patch on the wart
3. Tape firmly in place to ensure the patch does not slip or move

Warnings

Please keep out of reach of children.Do not swallow.Please clean your hands before use to ensure the best results from the product.Discontinue use if signs of irritation or rash occur.Store in a cool and dry place.

Do not use

Discontinue use if signs of irritation or rash occur.

Stop Use

Discontinue use if signs of irritation or rash occur.

KEEP OUT OF REACH OF CHILDREN

Please keep out of reach of children. Do not swallow.

STORAGE AND HANDLING

Store in a cool and dry place.

INACTIVE INGREDIENT

GLYCERIN